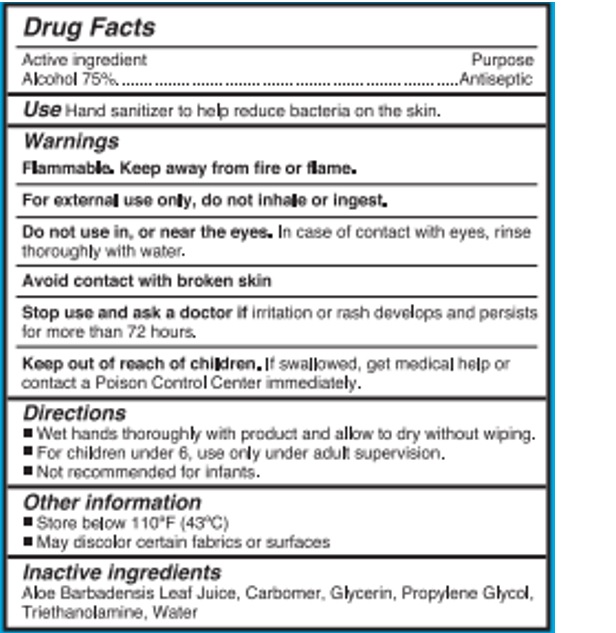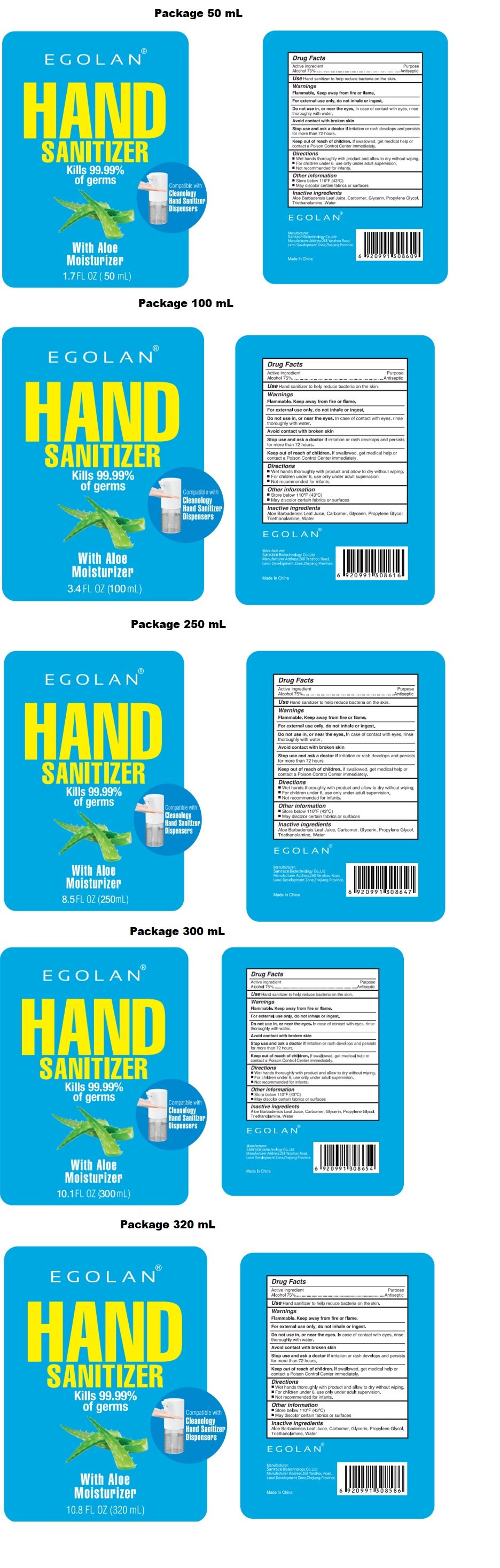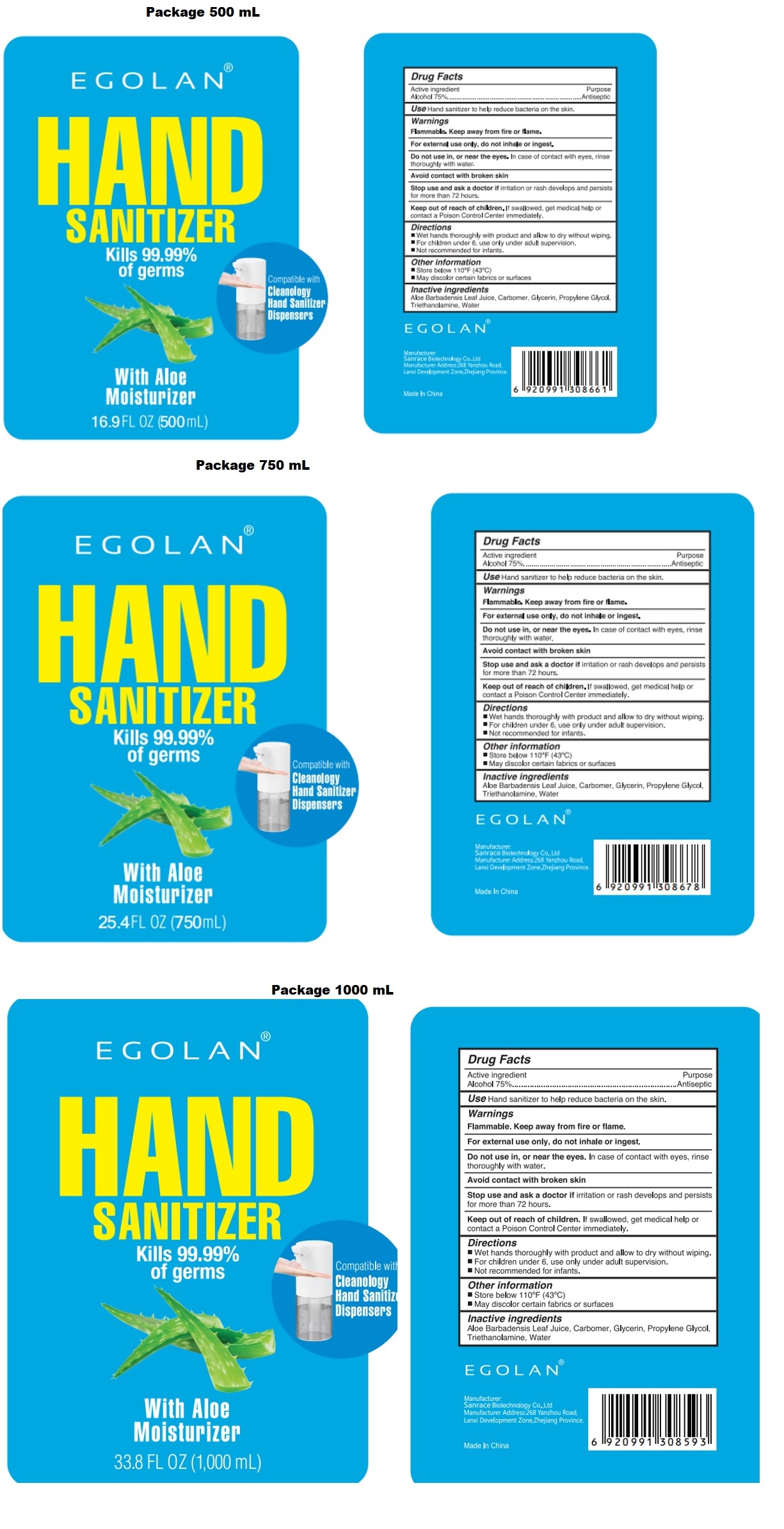 DRUG LABEL: EGOLAN HAND SANITIZER
NDC: 75448-028 | Form: GEL
Manufacturer: Sanrace Biotechnology Co., Ltd.
Category: otc | Type: HUMAN OTC DRUG LABEL
Date: 20201012

ACTIVE INGREDIENTS: ALCOHOL 75 mL/100 mL
INACTIVE INGREDIENTS: ALOE VERA LEAF; CARBOMER HOMOPOLYMER, UNSPECIFIED TYPE; GLYCERIN; PROPYLENE GLYCOL; TROLAMINE; WATER

EGOLAN® HAND SANITIZER

Active ingredient

Alcohol 75%

Purpose

Antiseptic

Use

Hand sanitizer to help reduce bacteria on the skin.

Warnings

Flammable. Keep away from fire or flame.

For external use only, do not inhale or ingest.

Do not use in, or near the eyes. In case of contact with eyes, rinse thoroughly with water.

Avoid contact with broken skin

Stop use ans ask a doctor if irritation or rash develops and persists for more than 72 hours.

Keep out of reach of children. If swallowed, get medical help or contact a Poison Control Center immediately.

Directions

- Wet hands thoroughly with product and allow to dry without wiping.
- For children under 6, use only under adult supervision.
- Not recommended for infants.

Other information

- Store below 110°F (43°C)
- May discolor certain fabrics or surfaces

Inactive ingredients

Aloe Barbadensis Leaf Juice, Carbomer, Glycerin, Propylene Glycol, Triethanolamine, Water

Kills 99.99% of germs

With Aloe Moisturizer

Compatible with Cleanology Hand Sanitizer Dispensers

Manufacturer: Sanrace Biotechnology Co.Ltd

manufacturer Address 268 Yanzhou Road, Lanxi Development Zone, Lanxi province

Made in China